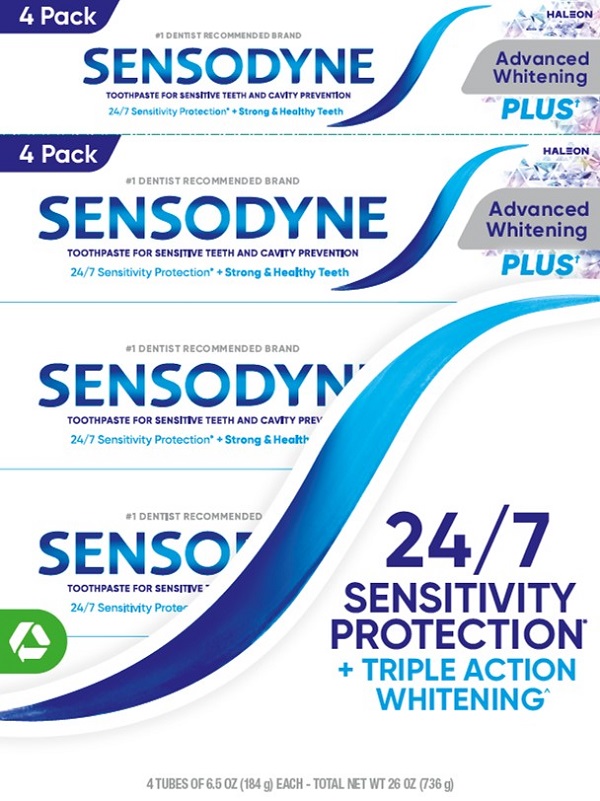 DRUG LABEL: SENSODYNE

NDC: 0135-5029 | Form: PASTE
Manufacturer: Haleon US Holdings LLC
Category: otc | Type: HUMAN OTC DRUG LABEL
Date: 20240712

ACTIVE INGREDIENTS: POTASSIUM NITRATE 50 mg/1 g; SODIUM FLUORIDE 1.11 mg/1 g
INACTIVE INGREDIENTS: WATER; SORBITOL; HYDRATED SILICA; GLYCERIN; SODIUM TRIPOLYPHOSPHATE ANHYDROUS; POLYETHYLENE GLYCOL 400; XANTHAN GUM; SODIUM METHYL COCOYL TAURATE; COCAMIDOPROPYL BETAINE; TITANIUM DIOXIDE; SODIUM HYDROXIDE; SACCHARIN SODIUM; SUCRALOSE

Drug Facts

Active ingredients

Potassium nitrate 5%

Sodium fluoride 0.25% (0.15% w/v fluoride ion)

Purposes

Antihypersensitivity

Anticavity

Uses

- builds increasing protection against painful sensitivity of the teeth to cold, heat, acids, sweets, or contact.
- aids in the prevention of dental cavities.

Warnings

Stop use and ask a dentist if

- the problem persists or worsens. Sensitive teeth may indicate a serious problem that may need prompt care by a dentist.
- pain/sensitivity still persists after 4 weeks of use.

Keep out of reach of children.

If more than used for brushing is accidentally swallowed, get medical help or contact a Poison Control Center right away.

Directions

- adults and children 12 years of age and older:
  - apply at least a 1-inch strip of the product onto a soft bristle toothbrush.
  - brush teeth thoroughly for at least 1 minute twice a day (morning and evening), and not more than 3 times a day, or as recommended by a dentist or doctor. Make sure to brush all sensitive areas of the teeth. Minimize swallowing. Spit out after brushing.
- children under 12 years of age:Consult a dentist or doctor.

Other information

- do not store above 25°C (77°F)

Inactive ingredients

water, sorbitol, hydrated silica, glycerin, pentasodium triphosphate, PEG-8, flavor, silica, xanthan gum, sodium methyl cocoyl taurate, cocamidopropyl betaine, titanium dioxide, sodium hydroxide, sodium saccharin, sucralose

Questions or comments?

1-866-844-2797

ALWAYS FOLLOW THE LABEL

Additional information

SENSODYNE

Advanced Whitening PLUS

What are sensitive teeth?

Lots of people have sensitive teeth. When enamel is worn away (through eating everyday acidic food or

drinks) or gums recede, the dentin underneath becomes exposed. This can lead to tooth sensitivity,

for example, with cold and hot food and drinks.

What does Sensodyne do?

Sensodyne provides daily care for sensitive teeth* plus all the benefits you would expect from a daily fluoride toothpaste - strong teeth and freshness.

helps remove stains for a whiter smile, while calming the nerves deep inside the tooth for 24 hour sensitivity relief*that helps keep the pain from coming back

24/7 Sensitivity Protection*

+ Triple Action Whitening

Use Sensodyne Advanced Whitening PLUS twice daily:

• Long lasting sensitivity protection*

+ Triple action whitening

- Removes stains
- Polishes enamel
- Prevents future stains

• Contains fluoride to protect against cavities

* with twice daily brushing

^ removes stains, polishes enamel,

and prevents future stains

† lower abrasivity vs Sensodyne

Advanced Whitening

CARTON RECYCLE

TUBE RECYCLE

CAP CHECK LOCALLY

†Recycling facilities for the cap may not exist in your area

Save Water

Turn off tap while brushing

Recyclable Packaging

Recyclable Carton

Recyclable Tube & Cap

Distributed by:

Haleon

Warren, NJ 07059

Trademarks owned or licensed by Haleon.

©2024 Haleon or licensor.

Pat. Info www.productpats.com

62000000209613

Principal Display Panel

4 Pack HALEON

#1 DENTIST RECOMMENDED BRAND

SENSODYNE

Advanced Whitening PLUS

TOOTHPASTE FOR SENSITIVE TEETH AND CAVITY PREVENTION

24/7 Sensitivity Protection* + Strong & Healthy Teeth

24/7 SENSITIVITY PROTECTION + TRIPLE ACTION WHITENING

4 TUBES OF 6.5 OZ (184 g) EACH - TOTAL NET WT 26 OZ (736 g)